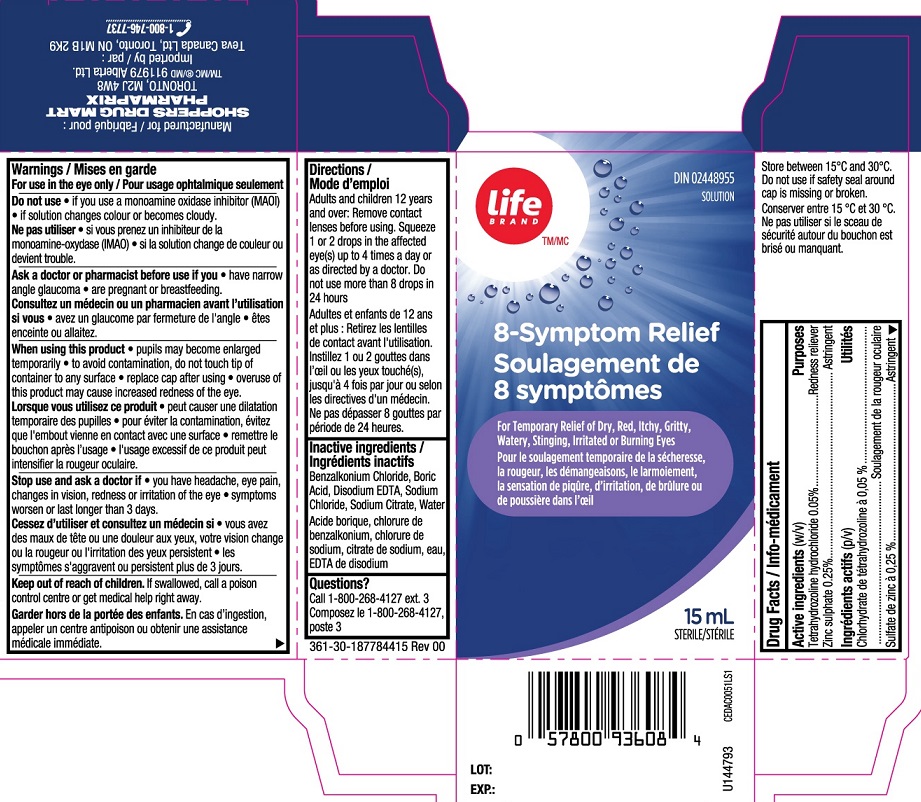 DRUG LABEL: Life Brand 8 Symptom Relief
NDC: 55651-046 | Form: SOLUTION
Manufacturer: KC Pharmaceuticals, Inc.
Category: otc | Type: HUMAN OTC DRUG LABEL
Date: 20251231

ACTIVE INGREDIENTS: TETRAHYDROZOLINE HYDROCHLORIDE 0.05 g/100 mL; ZINC SULFATE 0.25 g/100 mL
INACTIVE INGREDIENTS: BENZALKONIUM CHLORIDE; WATER; EDETATE DISODIUM; SODIUM CHLORIDE; SODIUM CITRATE; BORIC ACID

Life Brand 8 Symptom Relief 15 mL MFR